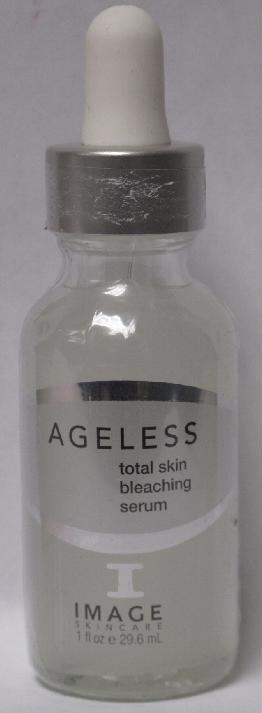 DRUG LABEL: AGELESS Total Skin Bleaching Serum
NDC: 62742-4033 | Form: LIQUID
Manufacturer: Allure Labs, Inc.
Category: otc | Type: HUMAN OTC DRUG LABEL
Date: 20100701

ACTIVE INGREDIENTS: HYDROQUINONE 20 mg/1 mL

Drug Facts

ACTIVE INGREDIENTS:
Hydroquinone: 2%

INACTIVE INGREDIENTS:

Water, Glycolic Acid, Citric Acid, Phytic Acid, Azelaic Acid, Aloe Barbedensis Leaf Extract, Phyenoxyethanol, Ethylhexylglycerin, Hexylene Glycol, Melaleuca Alternifolia (Tea Trea) Leaf Oil, Xanthan Gum, Mentha Virdis (Spearmint) Oil, Eucaluptus Globulus Leaf Oil, Glycyrrhiza Glabra (Licorice) Root Extract, Pineapple-Coconut Enzyme.

Other Information on the back of the container:

(Claims)

An oil-free hydroquinone/glycolic acid serum that gently lightens skin discolorations. Daily application lightens melasma, freckeles and other areas of melanin hyperpigmention.

Paraben-free

Directions:

Apply to cleansed skin morning and evening.

Indications:

Freckles, melasma, post pregnancy pigmentation disorders, hand discolorations.

Distributor:

Image International

Palm Beach, FL 33411 USA

www.imageskincare.com

Image of the Product (Front): AGELESS Total Skin Bleaching Serum